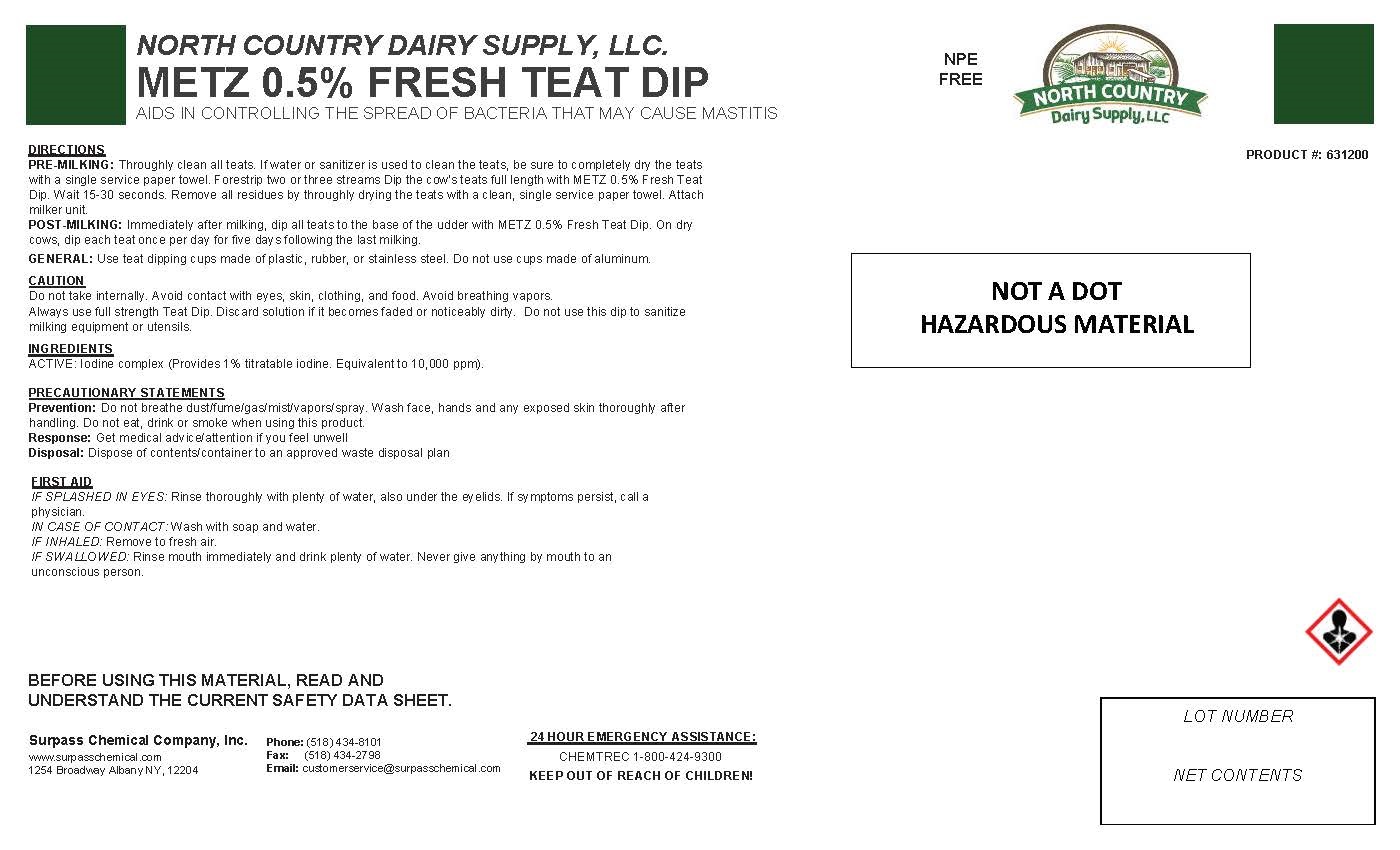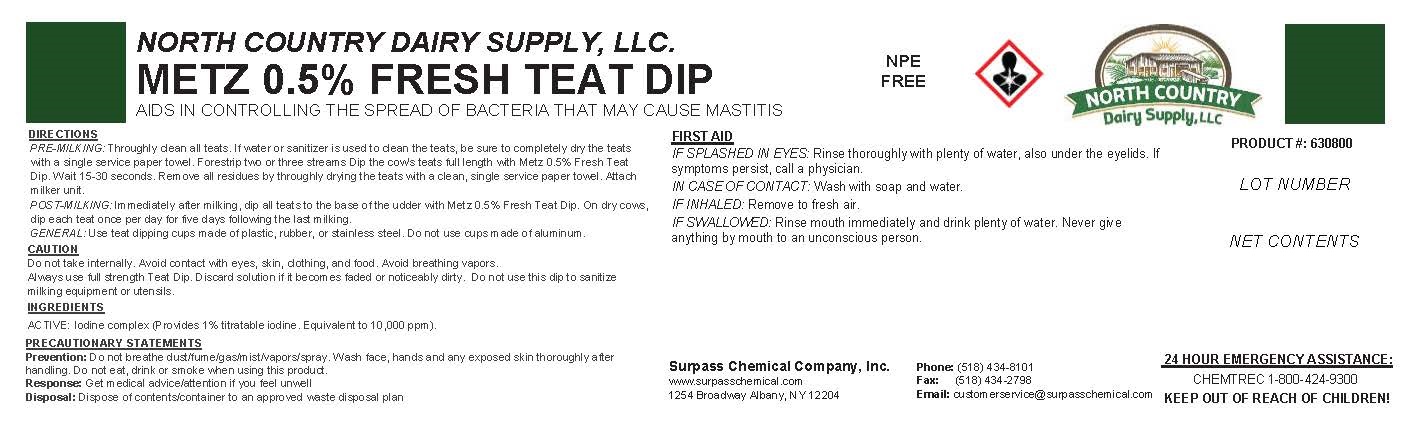 DRUG LABEL: Metz 0.5% Fresh Teat Dip
NDC: 86067-0021 | Form: SOLUTION
Manufacturer: Surpass Chemical Company, Inc.
Category: animal | Type: OTC ANIMAL DRUG LABEL
Date: 20221227

ACTIVE INGREDIENTS: IODINE 0.0275 g/1 g
INACTIVE INGREDIENTS: WATER 0.8787 g/1 g; C9-11 PARETH-8 0.0354 g/1 g; GLYCERIN 0.05 g/1 g; LAURETH-11 CARBOXYLIC ACID 0.0033 g/1 g; SODIUM HYDROXIDE 0.0021 g/1 g; ANHYDROUS CITRIC ACID 0.003 g/1 g

Metz 0.5% Fresh Teat Dip

DESCRIPTION

NORTH COUNTRY DAIRY SUPPLY, LLC. NPE

METZ 0.5% FRESH TEAT DIP FREE

AIDS IN CONTROLLING THE SPREAD OF BACTERIA THAT MAY CAUSE MASTITIS PRODUCT #: 630800

DIRECTIONS:
PRE-MILKING: Throughly clean all teats. If water or sanitizer is used to clean the teats, be sure to completely dry the teats with a single service paper towel. Forestrip two or three streams Dip the cow's teats full length with Metz Fresh 0.5% Teat Dip. Wait 15-30 seconds. Remove all residues by throughly drying the teats with a clean, single service paper towel. Attach milker unit.
POST-MILKING: Immediately after milking, dip all teats to the base of the udder with Metz Fresh 0.5% Teat Dip. On dry cows, dip each teat once per day for five days following the last milking.
GENERAL: Use teat dipping cups made of plastic, rubber, or stainless steel. Do not use cups made of aluminum.

GENERAL PRECAUTIONS

CAUTION:
Do not take internally. Avoid contact with eyes, skin, clothing, and food. Avoid breathing vapors.
Always use full strength Teat Dip. Discard solution if it becomes faded or noticeably dirty. Do not use this dip to sanitize
milking equipment or utensils

PRECAUTIONS

PRECAUTIONARY STATEMENTS
Prevention: Do not breathe dust/fume/gas/mist/vapors/spray Wash face, hands and any exposed skin thoroughly after
handling Do not eat, drink or smoke when using this product
Response: Get medical advice/attention if you feel unwell
Disposal: Dispose of contents/container to an approved waste disposal plant

OTHER SAFETY INFORMATION

FIRST AID:
IF SPLASHED IN EYES:Rinse thoroughly with plenty of water, also under the eyelids. If symptoms persist, call a physician.
IN CASE OF CONTACT: Wash with soap and water.
IF INHALED: Remove to fresh air.
IF SWALLOWED: Rinse mouth immediately and drink plenty of water. Never give anything by mouth to an unconscious person.

ACTIVE INGREDIENT

INGREDIENTS:
ACTIVE: Iodine complex (Provides 1% titratable iodine. Equivalent
to 10,000 ppm).

KEEP OUT OF REACH OF CHILDREN!

Surpass Chemical Company, Inc.
www.surpasschemical.com 24 HOUR EMERGENCY ASSISTANCE:
Phone: (518) 434-8101 1254 Broadway CHEMTREC 1-800-424-9300
Fax: (518) 434-2798 Albany NY, 12204
Email: customerservice@surpasschemical.com

BEFORE USING THIS MATERIAL, READ AND
UNDERSTAND THE CURRENT SAFETY DATA SHEET.